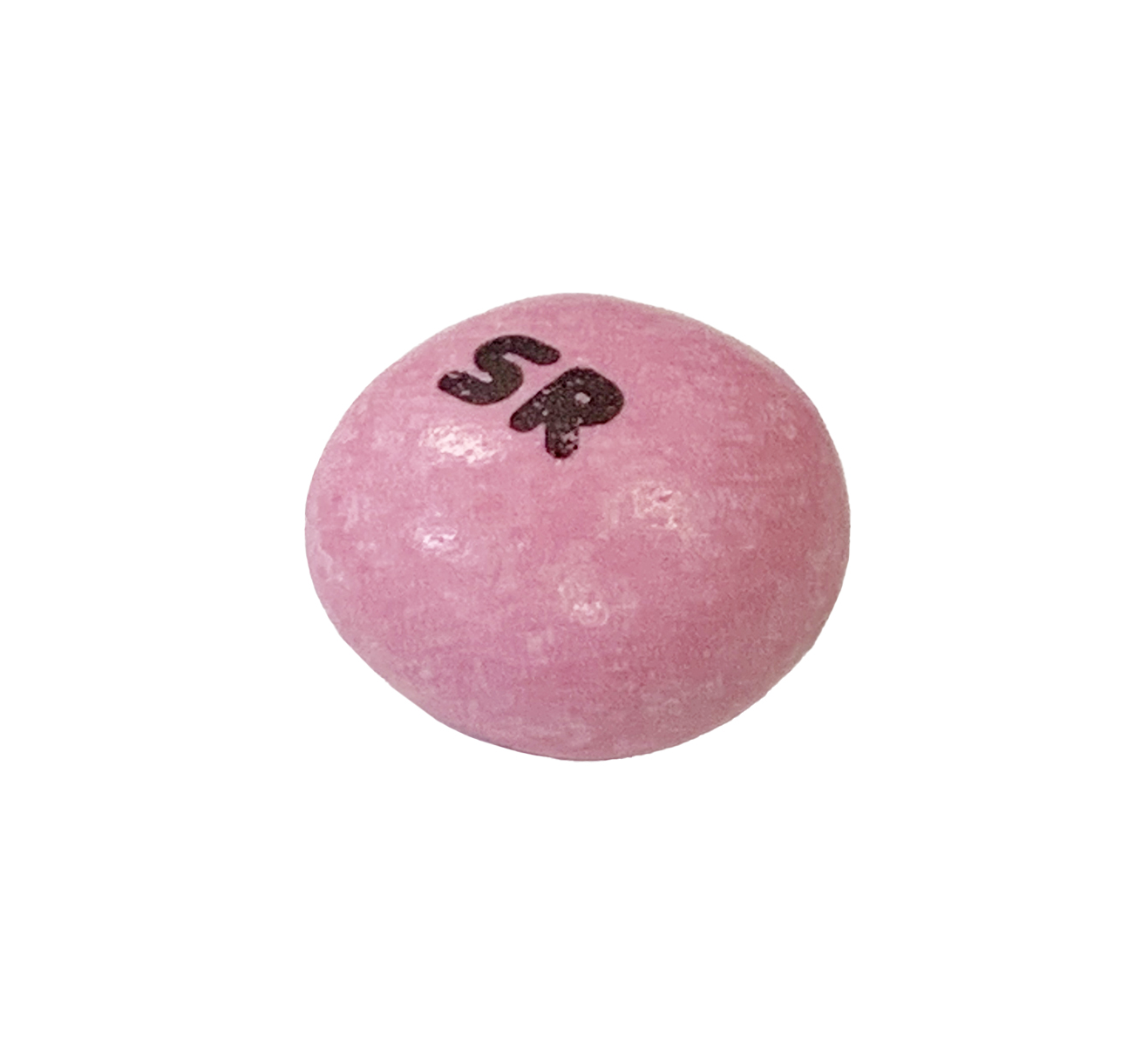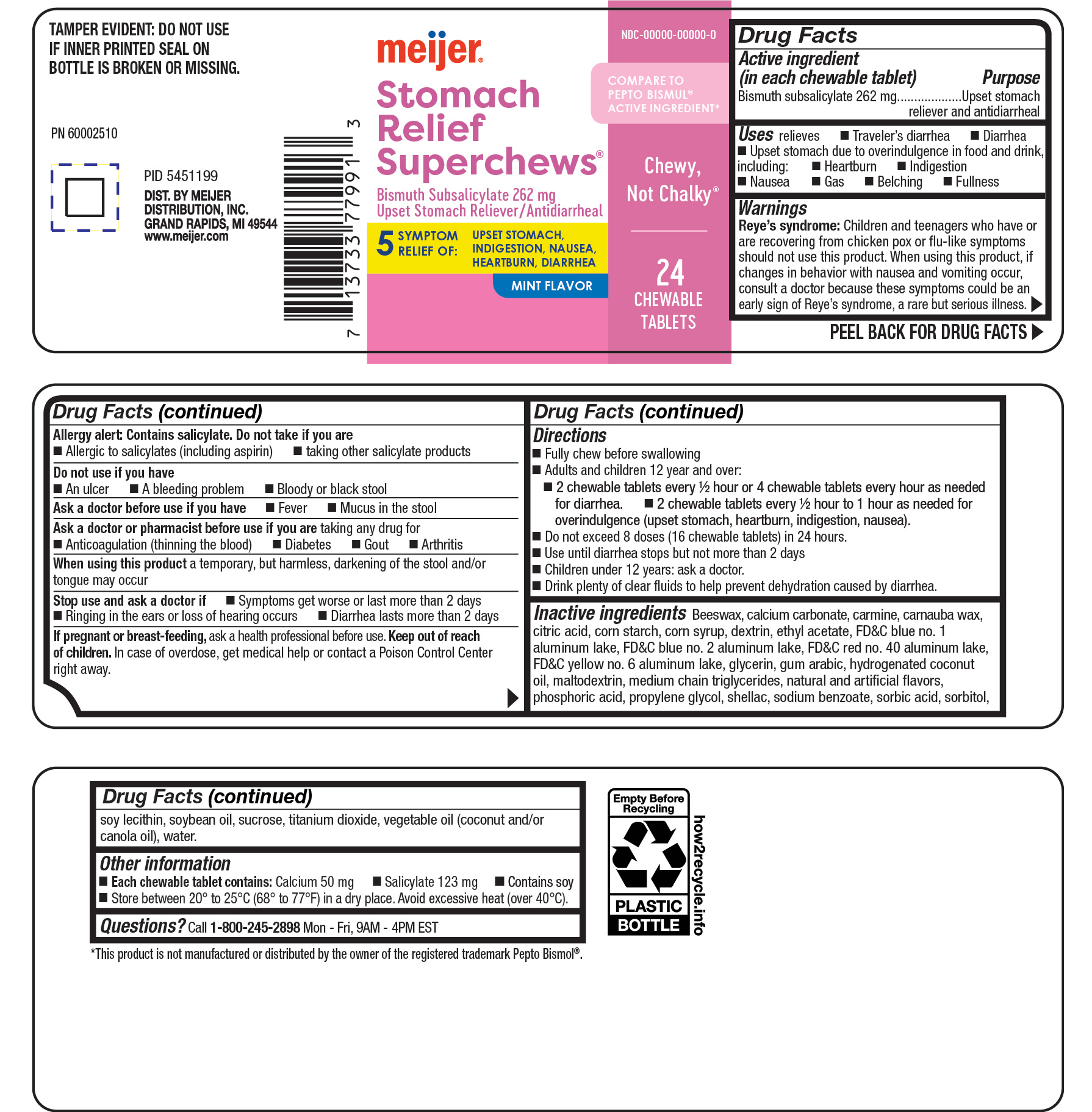 DRUG LABEL: Meijer Bismuth Stomach Relief
NDC: 79481-0097 | Form: TABLET, CHEWABLE
Manufacturer: Meijer
Category: otc | Type: HUMAN OTC DRUG LABEL
Date: 20251218

ACTIVE INGREDIENTS: BISMUTH SUBSALICYLATE 262 mg/1 1
INACTIVE INGREDIENTS: CALCIUM CARBONATE

Bismuth 262 mg

Active ingredient (in each chewable tablet)

Bismuth subsalicylate 262 mg

Purpose

Upset stomach reliever and antidiarrheal

INDICATIONS AND USAGE

Uses relieves

- Traveler's diarrhea
- Diarrhea
- Upset stomach due to overindulgence in food and drink, including
- Heartburn
- Indigestion
- Nausea
- Gas
- Belching
- Fullness

Warnings

Reye's syndrome: Children and teenagers who have or are recovering from chicken pox or flu-like symptoms should not use this product. When using this product, if changes in behavior with nausea and vomiting occur, consult a doctor because these symptoms could be an early sign of Reye's syndrome, a rare but serious illness.

Allergy alert: Contains salicylate. Do not take if you are

- Allergic to salicylates (including aspirin)
- taking other salicylates products

Do not use if you have

- An ulcer
- A bleeding problem
- Bloody or black stool

Ask a doctor before use if you have

- Fever
- Mucus in the stool

Ask a doctor or pharmacist before use if you are taking any drug for

- Anticoagulation (thinning the blood)
- Diabetes
- Gout
- Arthritis

When using this product a temporary, but harmless, darkening of the stool and/or tongue may occur

Stop use and ask a doctor if

- Symptoms get worse or last more than 2 days
- Ringing in the ears or loss of hearing occurs
- Diarrhea lasts more than 2 days

PREGNANCY OR BREAST FEEDING

If pregnant or breast-feeding, ask a health professional before use.

Keep out of reach of children.

OVERDOSAGE

In case of overdose, get medical help or contact a Poison Control Center right away.

Directions

- Fully chew before swallowing
- Adults and children 12 years abd over:
- 2 chewable tablets every 1/2 hour or 4 chewable tablets every hour as needed for diarrhea.
- 2 chewable tablets every 1/2 hour to 1 hour as needed for overindulgence (upset stomach, heartburn, indigenstion, nausea).
- Do not exceed 8 doses (16 chewable tablets) in 24 hours.
- Use until diarrhea stops but not more than 2 days
- Children under 12 years: ask a doctor.
- Drink plenty of clear fluids to help prevent dehydration caused by diarrhea.

INACTIVE INGREDIENT

Inactive ingredients: Beeswax, calcium carbonate, carmine, carnauba wax, citric acid, corn starch, corn syrup, dextrin, ethyl acetate, FD&C blue no. 1 aluminum lake, FD&C blue no. 2 aluminum lake, FD&C red no. 40 aluminum lake, FD&C yellow no. 6 aluminum lake, glycerin, gum arabic, hydrogenated coconut oil, maltodextrin, medium chain triglycerides, natural and artificial flavors, phosphoric acid, propylene glycol, shellac, sodium benzoate, sorbic acid, sorbitol, soy lecithin, soybean oil, sucrose, titanium dioxide, vegetable oil (coconut and/or canola oil), water.

Other information

- Each chewable tablet contains: Calcium 50mg
- Salicylate 123 mg
- Contains soy
- Store between 20° to 25°C (68° to 77°F) in a dry place. Avoid excessive heat (over40°C).

QUESTIONS

Questions? Call 1-800-245-2898 Mon - Fri, 9AM - 4PM EST